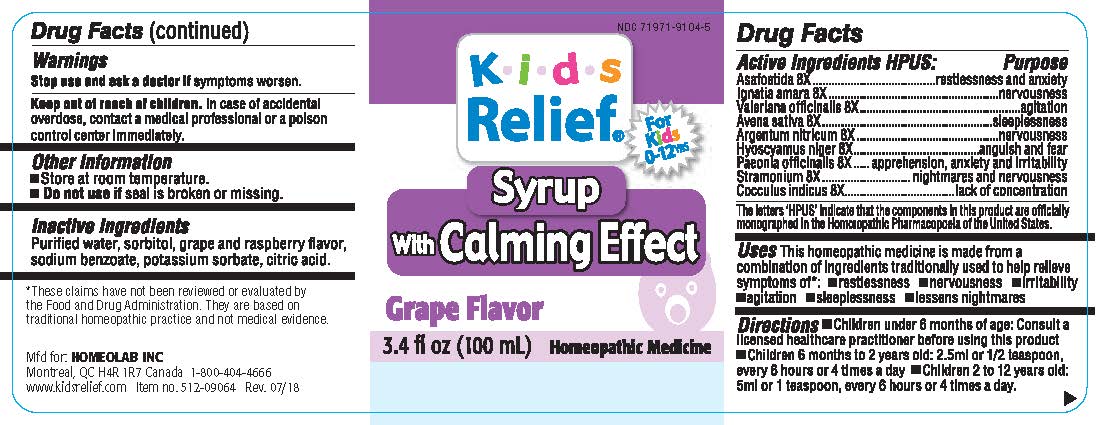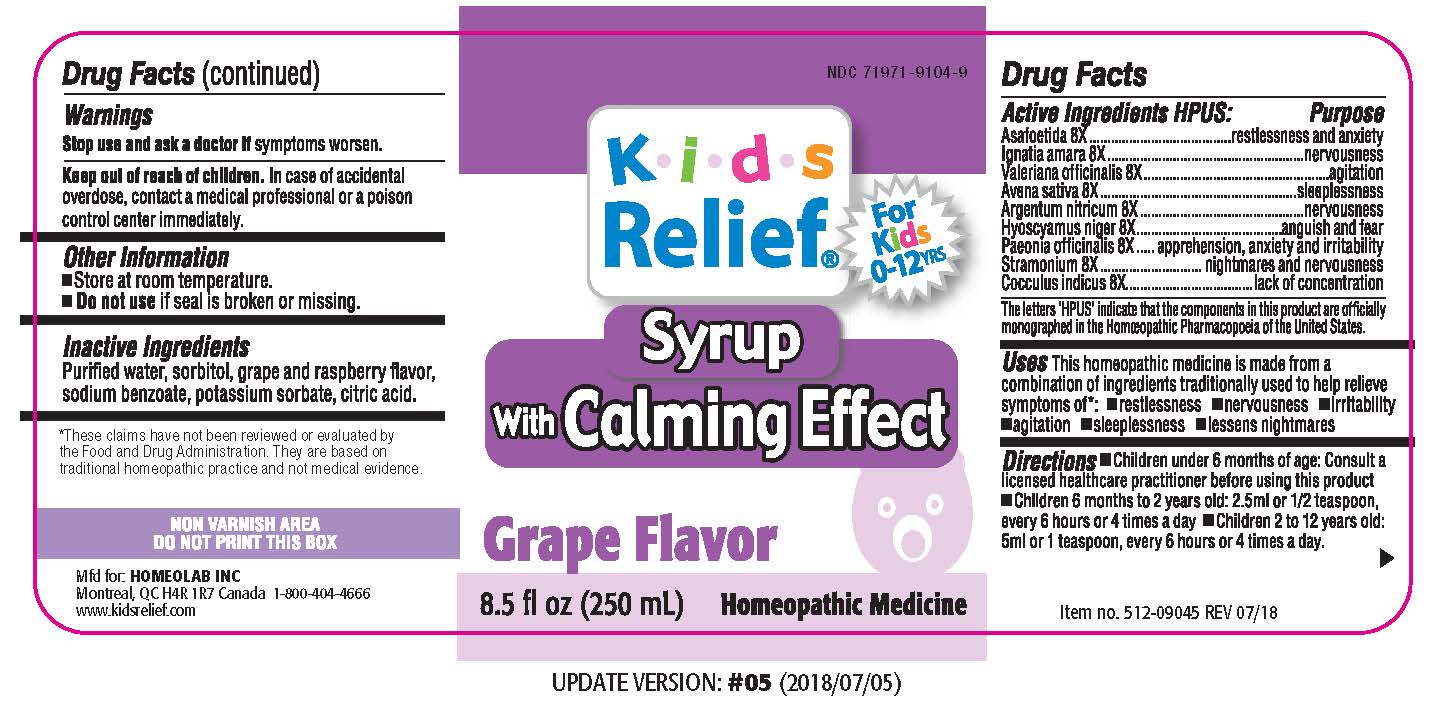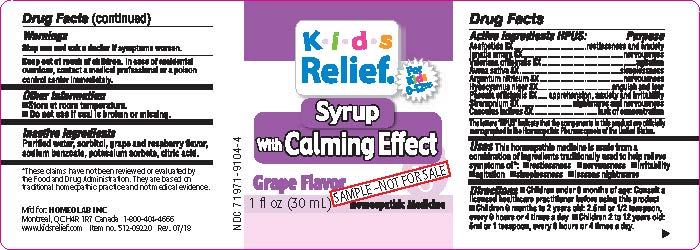 DRUG LABEL: Kids Relief
NDC: 63388-910 | Form: LIQUID
Manufacturer: Laboratoire Atlas Inc
Category: homeopathic | Type: HUMAN OTC DRUG LABEL
Date: 20251008

ACTIVE INGREDIENTS: ASAFETIDA 8 [hp_X]/100 mL; STRYCHNOS IGNATII SEED 8 [hp_X]/100 mL; VALERIANA OFFICINALIS WHOLE 8 [hp_X]/100 mL; OAT BRAN 8 [hp_X]/100 mL; SILVER NITRATE 8 [hp_X]/100 mL; HYOSCYAMUS NIGER 8 [hp_X]/100 mL; PAEONIA OFFICINALIS ROOT 8 [hp_X]/100 mL; DATURA STRAMONIUM 8 [hp_X]/100 mL; ANAMIRTA COCCULUS WHOLE 8 [hp_X]/100 mL
INACTIVE INGREDIENTS: WATER; SORBITOL; SODIUM BENZOATE; POTASSIUM SORBATE; CITRIC ACID MONOHYDRATE

Active Ingredients HPUS:

Asafo etida (Asafetida) 8 [HP_ X] in 100 mL.

Ignatia amara (Ig natius bean) 8 [ HP_X] in 100 mL.

Valeriana officinalis (Valerian) 8 [HP_ X] in a 100 mL.

Avena sativa (Oats) 8 [HP_X] in a 100 mL.

Argentum nitricum (Silver nitrate) 8 [HP_X] in a 100 mL.

Hyoscyamus niger (Henbane) 8 [HP_ X] in a 100 mL.

Paeonia officinalis (Peony) 8 [ HP_ X] in a 100 ml

Stramonium (Thorn apple) 8 [HP_ X] in a 100 mL.

Cocculus indicus (Indian berry) 8

Purpose of the Drug:

[e.g. sunscreen, analgesic, etc.] Purpose

Restlessness and anxiety

Nervousness. Agitation

Sleeplessness Anguish and fear

Apprehension, anxiety and irritability

Nightmares and nervousness

Lack of concentration

The letters 'HPUS' indicate that the components in this product are officially monographed in the

Homeopathic Pharmacopoeia of the United States.

*These claims have not been reviewed or evalauted by the Food and Drug Administration. They are based on traditional homeopathic practice not

medical evidence.

Uses

This homeopathic medicine is made from a combination of ingredients traditionally used to help relieve symptoms of:

Restlessness, nervousness, irritability, agitation, sleeplessness, lessens nightmares

•Uses

This homeopathic medicine is made from a combination of ingredients traditionally used to help relieve symptoms of:

•Restlessness •nervousness •irritability

•agitation •sleeplessness lessens nightmares

Warnings

Stop use and ask a doctor ifsymptoms worsen.

DOSAGE AND ADMINISTRATION

Directions •Children under 6 months of age: Consult a

licensed healthcare practitioner before using this product

•Children 6 months to 2 years old: 2.5 ml or 1.2 teaspoon,

every 6 hours or 4 times a day •Children 2 to 12 years old:

5ml or 1 teaspoon, every 6 hours or 4 times a day.

Keep out of reach of children. In case of accidental

overdose, contact a medical professional or a poison

control center immediately.

Other information

•Store at room temperature

• Do not useif seal is broken or missing

Inactive ingredients

Purified water, sorbitol, grape and rapsberry flavor,

sodium benzoate, potassium sorbate, citric acid.